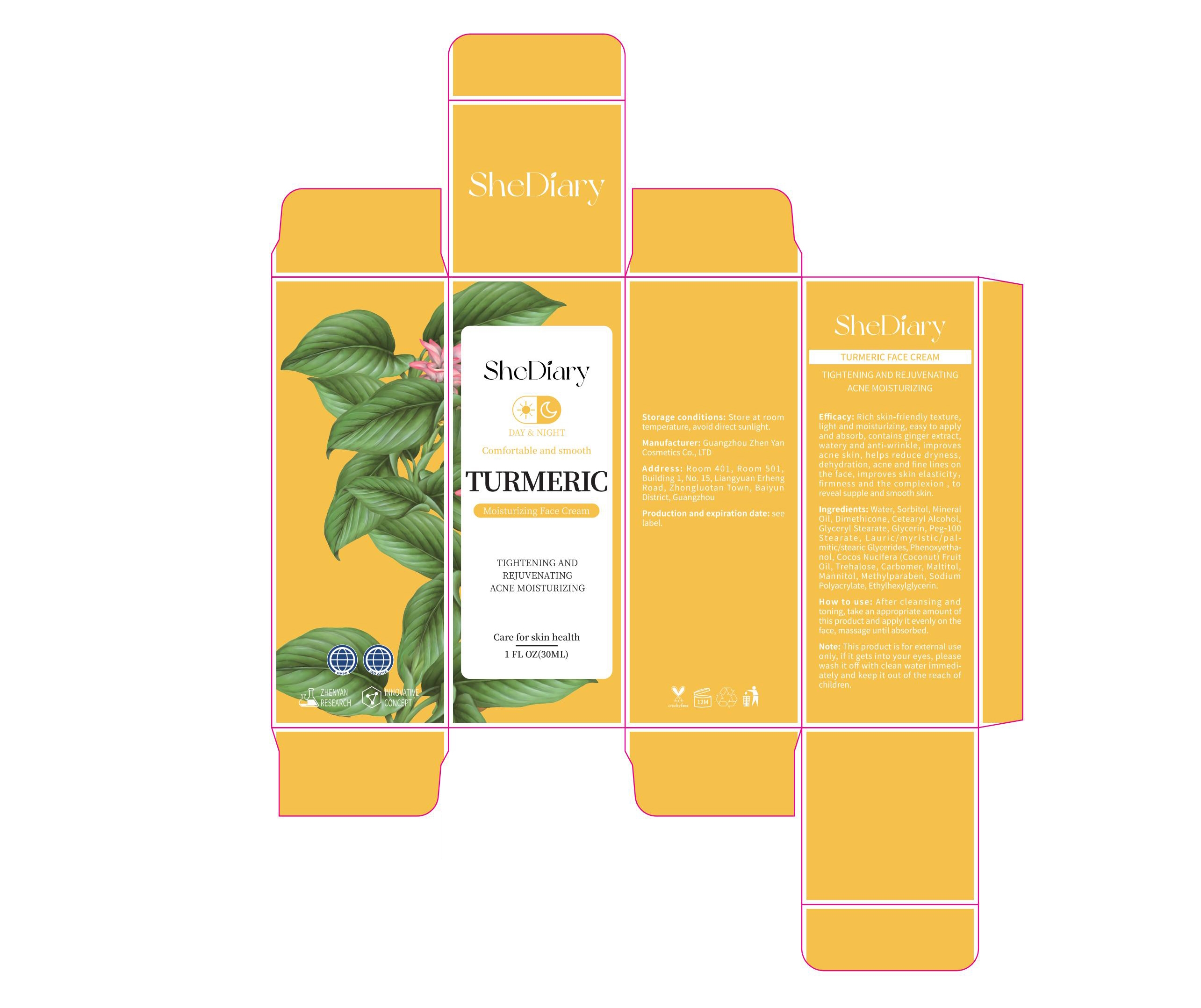 DRUG LABEL: shediary turmeric face cream
NDC: 84372-048 | Form: LOTION
Manufacturer: Shenzhen Zhumeng Times Technology Co., Ltd.
Category: otc | Type: HUMAN OTC DRUG LABEL
Date: 20240909

ACTIVE INGREDIENTS: SORBITOL 5 g/30 mL
INACTIVE INGREDIENTS: DIMETHICONE 6; PHENOXYETHANOL; MANNITOL; SODIUM; GLYCERIN; CETOSTEARYL ALCOHOL; PEG-100 STEARATE; MALTITOL; ETHYLHEXYLGLYCERIN; MINERAL OIL; GLYCERYL MONOSTEARATE; COCONUT OIL; WATER; TREHALOSE; METHYLPARABEN; LAURIC/MYRISTIC DIETHANOLOLAMIDE; IVERMECTIN

Active ingredients

Sorbitol 5%

Purpose

TIGHTENING AND REJUVENATINGACNE MOISTURIZING

Uses

After cleansing andtoning, take an appropriate amount ofthis product and apply it evenly on theface, massage until absorbed

Warnings

This product is for external useonly, if it gets into your eyes, pleasewash it off with clean water immedi-ately and keep it out of the reach ofchildren.

Dosage and administration

For external use only.

Do not use

Stop use and ask a doctor if

chest pain, rapid heartbeat, faintness, or dizziness occurs

sudden, unexplained weight gain occurs

your hands or feet swell

scalp irritation or redness occurs

unwanted facial hair growth occurs

you do not see hair regrowth in 4 months

May be harmful if used when pregnant or breast-feeding.

Keep out of reach of children, lf swallowed, get medical help or contact a Poison Control Center right away.

When using section

After cleansing andtoning, take an appropriate amount ofthis product and apply it evenly on theface, massage until absorbed

stop use

Broken or inflamed body

Keep out of reach of children

If sxralowed, get medical help or contact a Poison Conirol Cenler ngiht away.

Inactive ingredients

Water, MineralOil, Dimethicone, Cetearyl Alcohol,Glyceryl Stearate, Glycerin, Peg-100Stearate,Lauric/myristic/pal-mitic/stearic Glycerides, Phenoxyetha-nol, Cocos Nucifera(coconut) FruitOil, Trehalose,Carbomer, Maltitol.Mannitol, Methylparaben, sodiumPolyacrylate, Ethylhexylglycerin.